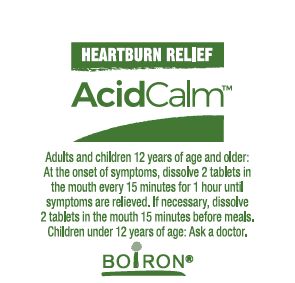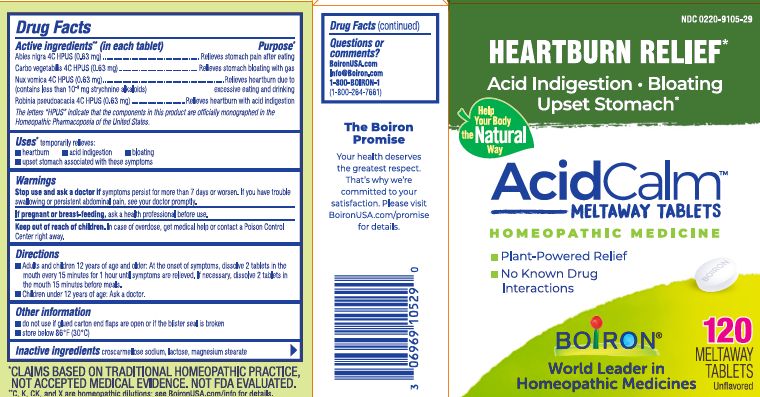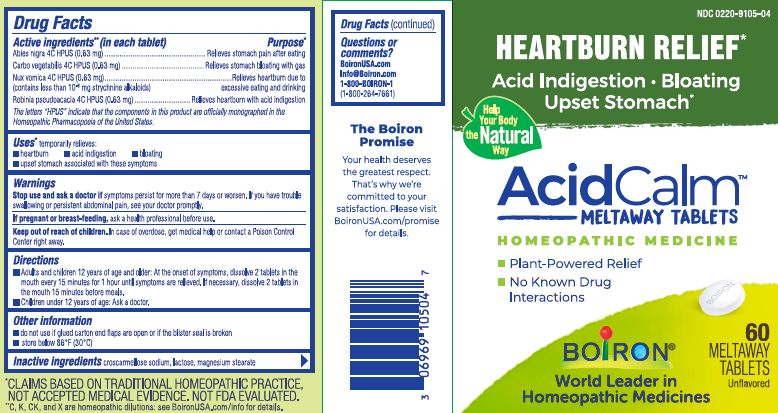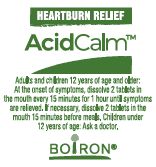 DRUG LABEL: AcidCalm
NDC: 0220-9105 | Form: TABLET
Manufacturer: Boiron
Category: homeopathic | Type: HUMAN OTC DRUG LABEL
Date: 20250215

ACTIVE INGREDIENTS: STRYCHNOS NUX-VOMICA SEED 4 [hp_C]/1 1; ROBINIA PSEUDOACACIA BARK 4 [hp_C]/1 1; PICEA MARIANA RESIN 4 [hp_C]/1 1; ACTIVATED CHARCOAL 4 [hp_C]/1 1
INACTIVE INGREDIENTS: LACTOSE; MAGNESIUM STEARATE; CROSCARMELLOSE SODIUM

AcidCalm tablets

Active ingredients** (in each tablet)

Abies nigra 4C HPUS (0.63 mg)

Carbo vegetabilis 4C HPUS (0.63 mg)

Nux vomica 4C HPUS (0.63 mg) (contains less than 10^-9 mg strychnine alkaloids)

Robinia pseudoacacia 4C HPUS (0.63 mg)

The letters "HPUS" indicate that the components in this product are officially monographed in the Homeopathic Pharmacopoeia of the United States.

Purpose*

Abies nigra 4C HPUS (0.63 mg)..................................................Relieves stomach pain after eating
Carbo vegetabilis 4C HPUS (0.63 mg).......................................Relieves stomach bloating with gas
Nux vomica 4C HPUS (0.63 mg)................. Relieves heartburn due to excessive eating and drinking
Robinia pseudoacacia 4C HPUS (0.63 mg)........................Relieves heartburn with acid indigestion

Uses*

Temporarily relieves:

- heartburn
- acid indigestion
- bloating
- upset stomach associated with these symptoms

Stop use and ask a doctor if symptoms persist for more than 7 days or worsen. If you have trouble swallowing or persistent abdominal pain, see your doctor promptly.

PREGNANCY OR BREAST FEEDING

If pregnant or breast-feeding, ask a health professional before use.

Keep out of reach of children. In case of overdose, get medical help or contact a Poison Control Center right away.

DOSAGE AND ADMINISTRATION

Adults and children 12 years of age and older: At the onset of symptoms, dissolve 2 tablets in the mouth every 15 minutes for 1 hour until symptoms are relieved. If necessary, dissolve 2 tablets in the mouth 15 minutes before meals.

Children under 12 years of age: Ask a doctor.

INACTIVE INGREDIENT

croscarmellose sodium, lactose, magnesium stearate

QUESTIONS

BoironUSA.com
Info@Boiron.com
1-800-BOIRON-1
(1-800-264-7661)
Made in France
Distributed by Boiron Inc.
Newtown Square, PA 19073

do not use if glue carton flaps are open or if the blister seal is broken

store below 86°F (30°C)

Heartburn relief*

Acid Indigestion Upset Stomach*

No Known Drug Interactions

60 Meltaway Tablets unflavored

120 Meltaway Tablets unflavored

*CLAIMS BASED ON TRADITIONAL HOMEOPATHIC PRACTICE, NOT ACCEPTED MEDICAL EVIDENCE. NOT FDA EVALUATED.

**C, K, CK, and X are homeopathic dilutions: see BoironUSA.com/info for details.